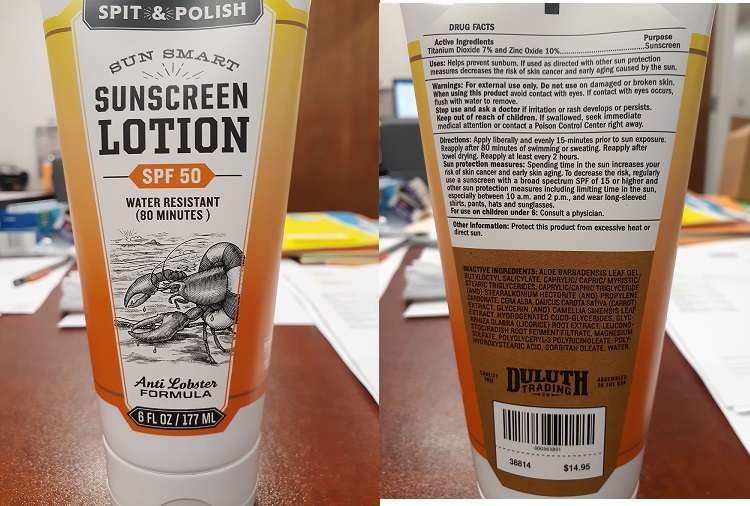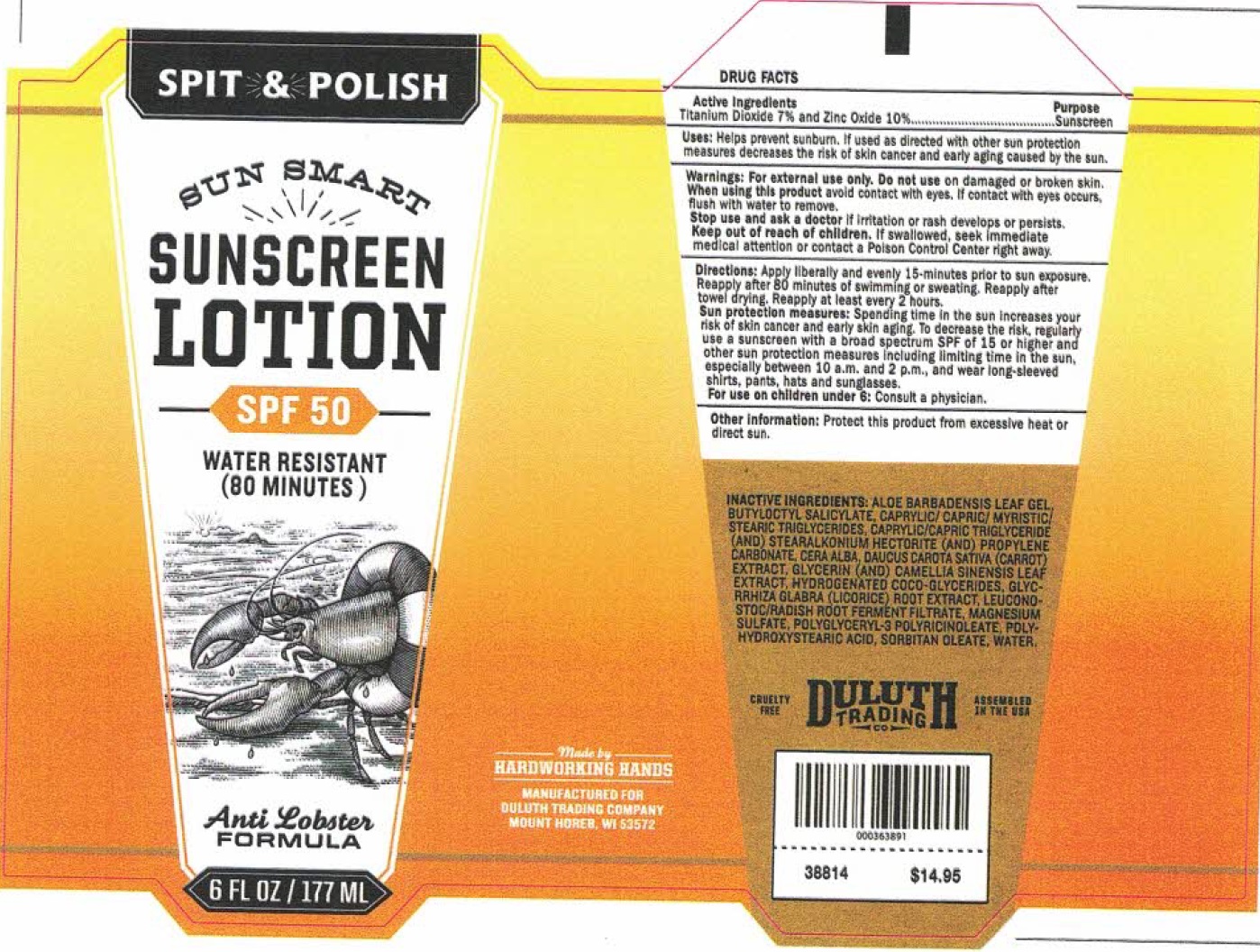 DRUG LABEL: Spit and Polish Sun Smart Sunscreen
NDC: 80325-001 | Form: LOTION
Manufacturer: Naturally Uncommon, LLC
Category: otc | Type: HUMAN OTC DRUG LABEL
Date: 20231109

ACTIVE INGREDIENTS: TITANIUM DIOXIDE 70 mg/1 mL; ZINC OXIDE 100 mg/1 mL
INACTIVE INGREDIENTS: ALOE VERA LEAF; BUTYLOCTYL SALICYLATE; GLYCERYL TRISTEARATE; MEDIUM-CHAIN TRIGLYCERIDES; STEARALKONIUM HECTORITE; PROPYLENE CARBONATE; WHITE WAX; CARROT; GLYCERIN; GREEN TEA LEAF; HYDROGENATED COCO-GLYCERIDES; GLYCYRRHIZA GLABRA; LEUCONOSTOC/RADISH ROOT FERMENT FILTRATE; MAGNESIUM SULFATE, UNSPECIFIED FORM; SORBITAN MONOOLEATE; WATER

Spit & Polish Sun Smart Sunscreen Lotion SPF 50

Active Ingredients

Titanium Dioxide 7% and Zinc Oxide 10%

Purpose

Sunscreen

Uses:

Helps prevent sunburn. If used as directed with other sun protection measures decreases the risk of skin cancer and early aging caused by the sun.

Warning:

For external use only.

Do not use

on damaged or broken skin.

When using this product

avoid contact with eyes, contact with eyes occurs, flush with water to remove.

Stop use and ask a doctor

If irritation or rash develops or persists.

Keep out of reach of children.

If swallowed, seek immediate medical attention of contact a Poison Control Center right away.

Directions:

Apply liberally and evenly 15 minutes prior to sun exposure. Reapply after 80 minutes of swimming or sweating Reapply after towel drying. Reapply at least every 2 hours.

Spending time in the sun increases your risk of skin cancer and early skin aging. To decrease the risk, regularly use a sunscreen with a broad spectrum SPF of 15 or higher and other sun protection measures including limiting time in the sun. especially between 10 a.m. and 2 pm, and wear long-sleeved shirts, pants, hats and sunglasses. Sun protection measures:

: Consult a physician. For use on children under 6

Other information:

Protect this product from excessive heat or direct sun.

INACTIVE INGREDIENTS:

ALOE BARBADENSIS LEAF GEL,BUTYLOCTYL SALICYLATE, CAPRYLIC/ CAPRIC/ MYRISTIC/STEARIC TRIGLYCERIDES, CAPRYLIC/CAPRIC/TRIGLYCERIDE (AND) STEARALKONIUM HECTORITE (AND) PROPYLENE CARBONATE, CERA ALBA, DAUCUS CAROTA SATIVA (CARROT) EXTRACT, GLYCERIN (AND) CAMELLIA SINENSIS LEAF EXTRACT, HYDROGENATED COCO-GLYCERIDES, GLYCRRHIZA GLABRA (LICORICE) ROOT EXTRACT, LEUCONO STOC/RADISH ROOT FERMENT FILTRATE, MAGNESIUM SULFATE. POLYGLYCERYL 3 POLYRICINOLEATE, POLY- HYDROXYSTEARIC ACID, SORBITAN OLEATE, WATER.